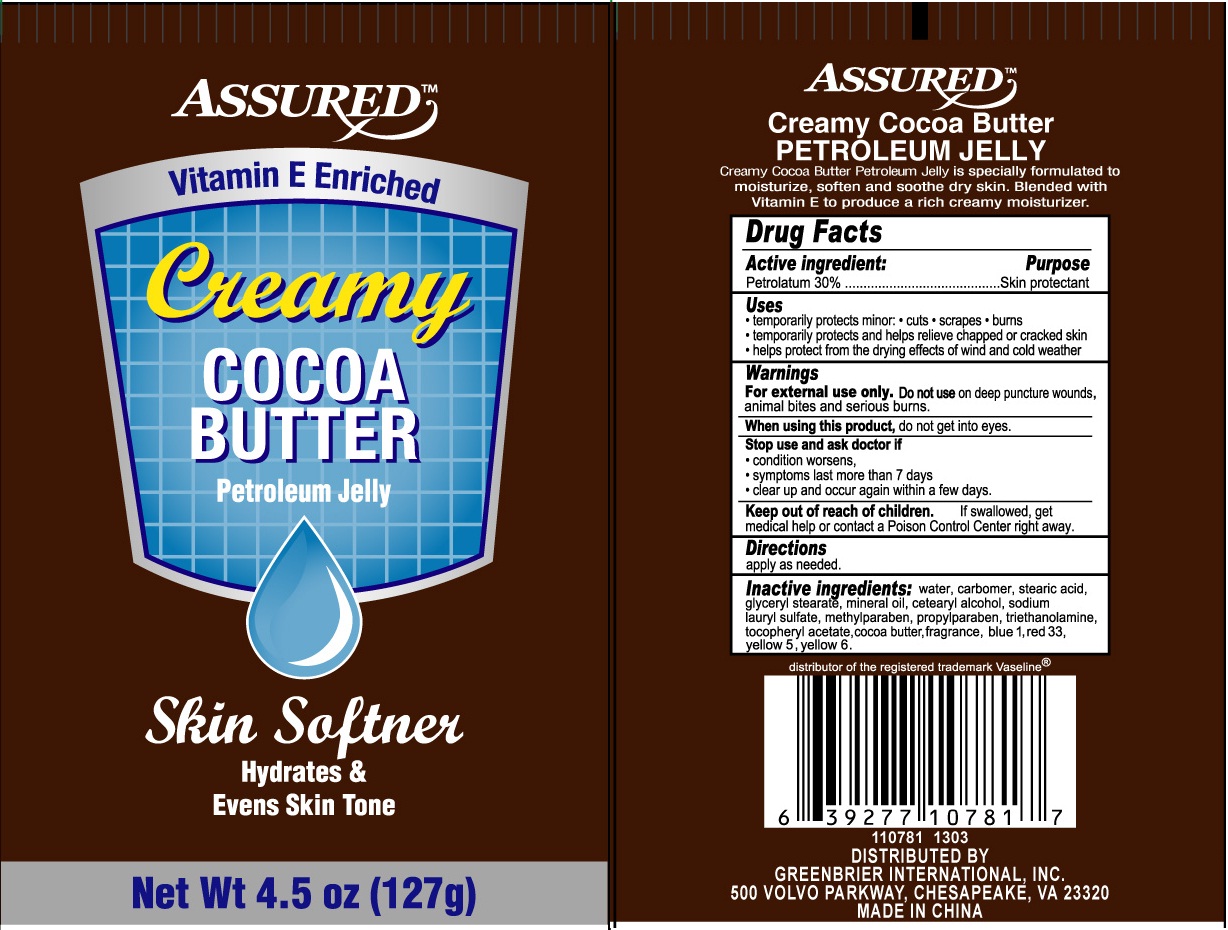 DRUG LABEL: Assured Creamy Cocoa Butter Petroleum Vitamin E Enriched
NDC: 33992-1310 | Form: JELLY
Manufacturer: GREENBRIER INTERNATIONAL
Category: otc | Type: HUMAN OTC DRUG LABEL
Date: 20130425

ACTIVE INGREDIENTS: PETROLATUM 30 g/100 g
INACTIVE INGREDIENTS: WATER; STEARIC ACID; GLYCERYL MONOSTEARATE; MINERAL OIL; CETOSTEARYL ALCOHOL; METHYLPARABEN; PROPYLPARABEN; TROLAMINE; COCOA BUTTER; FD&C YELLOW NO. 5; FD&C YELLOW NO. 6; D&C RED NO. 33; FD&C BLUE NO. 1

Drug Fact

PETROLEUM JELLY

Creamy petroleum Jelly is specially formulated to moisturize, soften and soothe dry skin. Blended with Vitamin E to produce a rich creamy moisturizer. Use on hands, knees, feet and heels to smooth away dryness.

DRUG FACTS

Active Ingredient Purpose

Petrolatum 30% Skin Protectant

Purpose

Skin Protectant

INDICATIONS AND USAGE

temporarily protects minor:

cuts scrapes burns

Temporarily protects and helps relieve chapped or cracked skin

Helps protect from the drying effects of wind and cold weather

Warnings

For external use only. Do not use on deep puncture wounds, animal bites and serious burns.

When using this product, do not get into eyes

Stop use and ask doctor if

condition worsens

Symptoms last more than 7 days

clear up and occur again within a few days.

Keep out of reach of children. If swallowed, get medical help or contact a Poison Control Center right away.

DOSAGE AND ADMINISTRATION

Directions: apply as needed

Inactive ingredients:

water (Aqua), Carbopol 940, Stearic Acid, Glyceryl Monostearate, Mineral Oil, Cetearyl Alcohol, GE125 Emulsifying Agent, Methylparaben, Propyparaben, Triethanolamine, Tocopheryl Acetate, Cocoa Butter, Fragrance,Yellow 5, Yellow 6, Red 33, Blue 1.

*This product is not manufactured or distributed by Unilever, distributor of the registered trademark Vaseline (r)

DISTRIBUTED BY:

GREENBRIER INTERNATIONAL, INC

CHESAPEAKE VA 23320

MADE IN CHINA